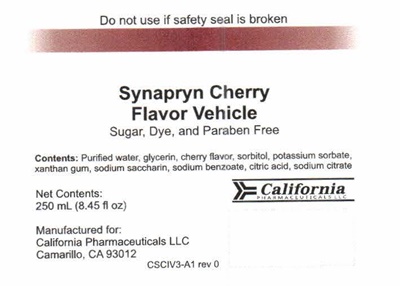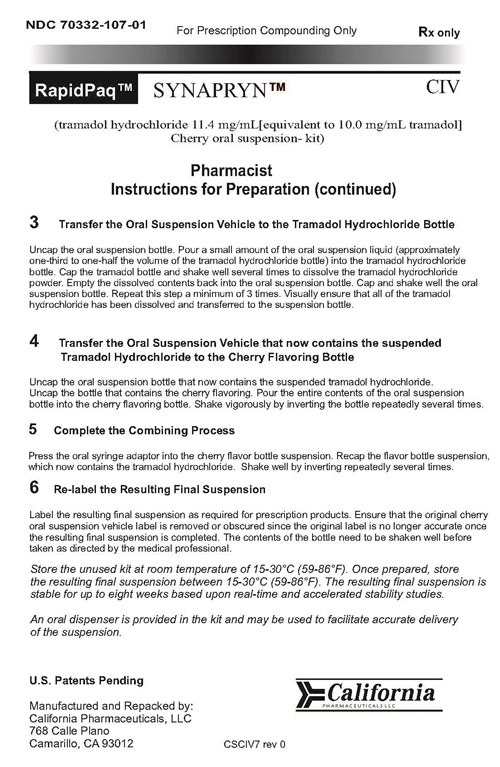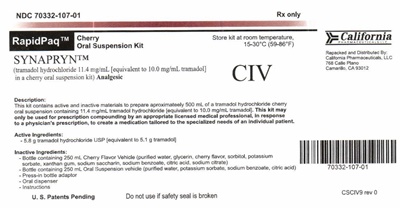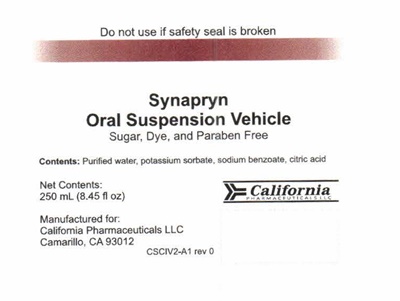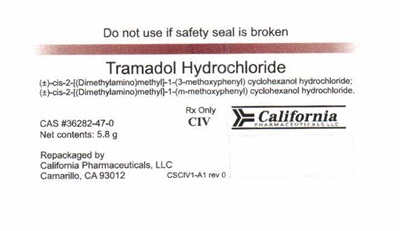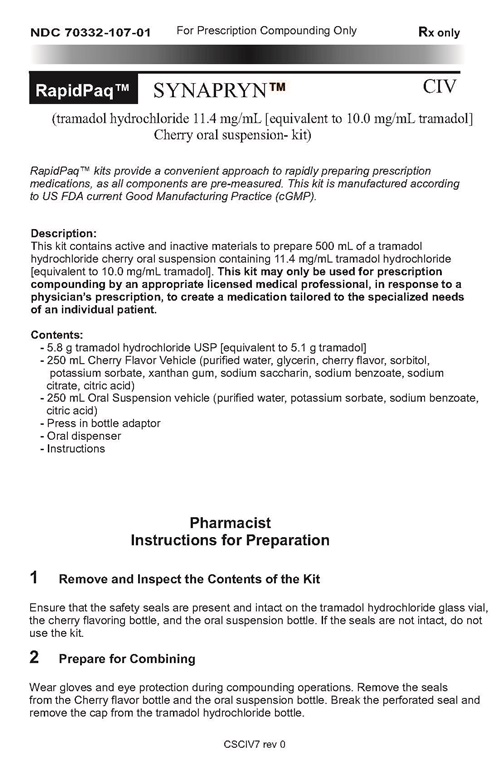 DRUG LABEL: SYNAPRYN
NDC: 70332-107 | Form: KIT | Route: ORAL
Manufacturer: California Pharmaceuticals, LLC
Category: prescription | Type: HUMAN PRESCRIPTION DRUG LABEL
Date: 20170807

ACTIVE INGREDIENTS: TRAMADOL HYDROCHLORIDE 5.8 g/5.8 g
INACTIVE INGREDIENTS: WATER; POTASSIUM SORBATE; SODIUM BENZOATE; CITRIC ACID MONOHYDRATE; WATER; GLYCERIN; SORBITOL; POTASSIUM SORBATE; XANTHAN GUM; SACCHARIN SODIUM; SODIUM BENZOATE; CITRIC ACID MONOHYDRATE; SODIUM CITRATE

Synapryn 107

Pharmacist Instructions For Preparation

1 Remove and Inspect the Contents of the Kit

Ensure that the safety seals are present and intact on the tramadol hydrochloride glass vial, the cherry flavoring bottle, and the oral suspension bottle. If the seals are not intact, do not use the kit.

2 Prepare for Combining

Wear gloves and eye protection during the compounding operations. Remove the seals from the Cherry flavor bottle and the oral suspension bottle. Break the perforated seal and remove the cap from the tramadol hydrochloride bottle.

3 Transfer the Oral Suspension Vehicle to the Tramadol Hydrochloride Bottle

Uncap the oral suspension bottle. Pour a small amount of the oral suspension liquid (approximately one-third to one-half the volume of the tramadol hydrochloride bottle) into the tramadol hydrochloride bottle. Cap the tramadol bottle and shake well several times to dissolve the tramadol hydrochloride powder. Empty the dissolved contents back into the oral suspension bottle. Cap and shake well the oral suspension bottle. Repeat this step a minimum of 3 times. Visually ensure that all of the tramadol hydrochloride has been dissolved and transfered to the suspension bottle.

4 Transfer the Oral Suspension Vehicle that now contains the suspended Tramadol Hydrochloride to the Cherry Flavoring Bottle

Uncap the oral suspension bottle that now contains the suspended tramadol hydrochloride. Uncap the bottle that contains the cherry flavoring. Pour the entire contents of the oral suspension bottle into the cherry flavoring bottle. Shake vigorously by inverting the bottle repeatedly several times.

5 Complete the Combining Process

Press the oral syringe adaptor into the cherry flavor bottle suspension. Recap the flavor bottle suspension, which now contains the tramadol hydrochloride. Shake well by inverting repeatedly several times.

6 Re-label the Resulting Final Suspension

Label the resulting final suspension as required for prescription products. Ensure that the original cherry oral suspension vehicle label is removed or obscured since the original label is no longer accurate once the resulting final suspension is completed. The contents of the bottle need to be shaken well before taken as directed by the medical professional.

Store the unused kit at room temperature of 15-30°C (59-86°F). Once prepared, store the resulting final suspension between 15-30°C (59-86°F). The resulting final suspension is stable for up to eight weeks based upon the real-time and accelerated stability studies.

An oral dispenser is provided in the kit and may be used to facilitate the accurate delivery of the suspension.

U.S. Patents Pending

Manufactured and repacked by:
California Pharmaceuticals, LLC
768 Calle Plano
Camarillo, CA 93012

CSCIV7 rev 0

Label

Synapryn - 107 product label

NDC 70332-107-01 For Prescription Compounding Only Rx only

RapidPaq™ SYNAPRYN™ CIV

(tramadol hydrochloride 11.4 mg/mL [equivalent to 10.0 mg/mL tramadol] Cherry oral suspension-kit)

RapidPaq™ kits provide a convenient approach to rapidly prepare prescription medications, as all components are pre-measured. This kit is manufactured according to the US FDA current Good Manufacturing Practice (cGMP).

Description
This kit contains active and inactive materials to prepare 500 mL of a tramadol hydrochloride cherry oral suspension containing 11.4 mg/mL tramadol hydrochloride [equivalent to 10.0 mg/mL tramadol]. This kit may only be used for prescription compounding by an appropriate licensed medical professional, in response to a physician's prescription, to create a medication tailored to the specific needs of an individual patient.

Contains:

- 5.8 g tramadol hydrochloride USP [equivalent to 5.1 g tramadol]

- 250 mL Cherry Flavor Vehicle (purified water, glycerin, cherry flavor, sorbitol, potassium sorbate, xanthan gum, sodium saccharin, sodium benzoate, sodium citric acid)

- 250 mL Oral Suspension vehicle (purified water, potassium sorbate, sodium benzoate, citric acid)

- Press in bottle adaptor

- Oral dispenser

- Insructions